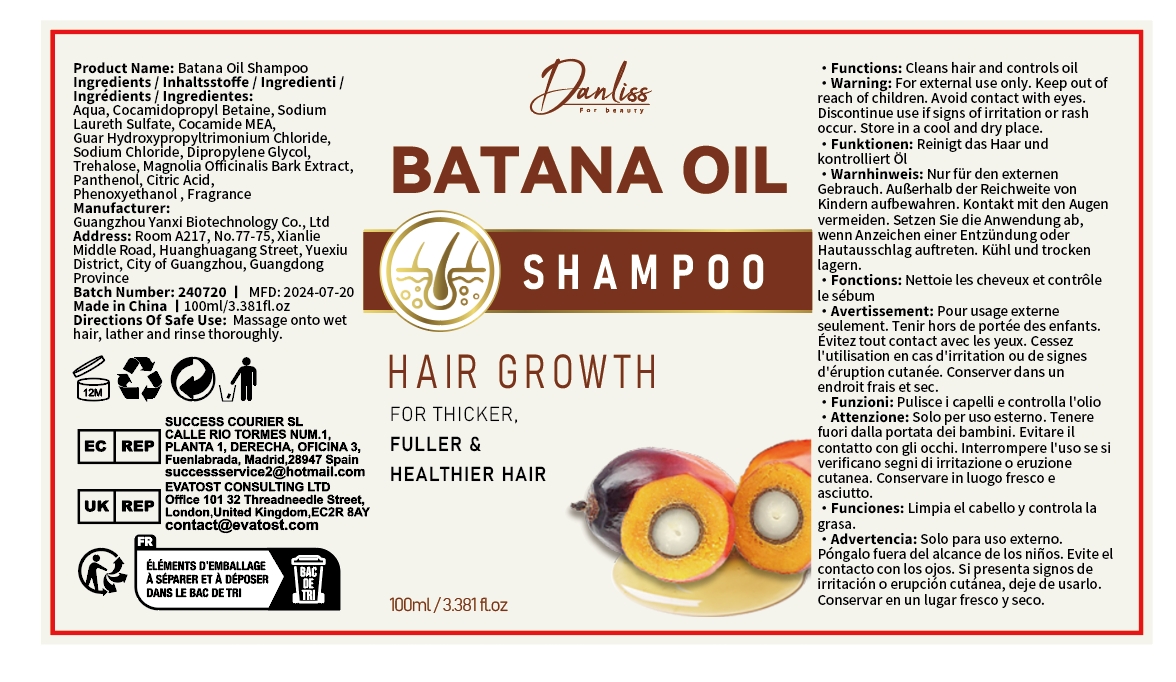 DRUG LABEL: Batana OilShampoo
NDC: 84025-203 | Form: CREAM
Manufacturer: Guangzhou Yanxi Biotechnology Co., Ltd
Category: otc | Type: HUMAN OTC DRUG LABEL
Date: 20241008

ACTIVE INGREDIENTS: COCAMIDOPROPYL BETAINE 5 mg/100 mL
INACTIVE INGREDIENTS: WATER

DOSAGE AND ADMINISTRATION

USE AS A NORMAL HAIR CREAM

WARNINGS

Keep out of children

INACTIVE INGREDIENT

Aqua

INDICATIONS AND USAGE

Used for hair cleaning

Keep out of children

PURPOSE

Clean, fluffy, moisturizing hair